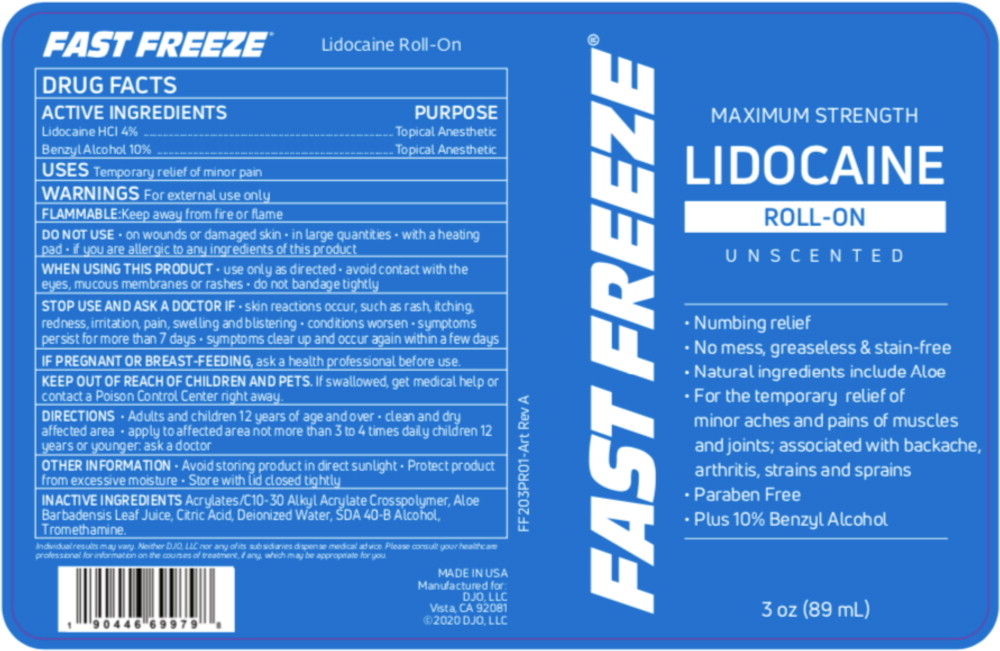 DRUG LABEL: Fast Freeze Lidocaine Roll-On
NDC: 66902-235 | Form: LIQUID
Manufacturer: Natural Essentials, Inc.
Category: otc | Type: HUMAN OTC DRUG LABEL
Date: 20241004

ACTIVE INGREDIENTS: LIDOCAINE HYDROCHLORIDE 40 mg/1 mL; BENZYL ALCOHOL 10 mg/1 mL
INACTIVE INGREDIENTS: CARBOMER COPOLYMER TYPE A (ALLYL PENTAERYTHRITOL CROSSLINKED); ALOE VERA LEAF; CITRIC ACID MONOHYDRATE; WATER; ALCOHOL; TROLAMINE

DRUG FACTS

ACTIVE INGREDIENTS

Lidocaine HCl 4%

Benzyl Alcohol 10%

PURPOSE

Topical Anesthetic

Topical Anesthetic

USES

Temporary relief of minor pain

WARNINGS

For external use only

FLAMMABLE:Keep away from fire or flame

DO NOT USE

- on wounds or damaged skin
- in large quantities
- with a heating pad
- if you are allergic to any ingredients of this product

WHEN USING THIS PRODUCT

- use only as directed
- avoid contact with the eyes, mucous membranes or rashes
- do not bandage tightly

STOP USE AND ASK A DOCTOR IF

- skin reactions occur, such as rash, itching, redness, irritation, pain, swelling and blistering
- conditions worsen
- symptoms persist for more than 7 days
- symptoms clear up and occur again within a few days

PREGNANCY OR BREAST FEEDING

IF PREGNANT OR BREAST-FEEDING, ask a health professional before use.

KEEP OUT OF REACH OF CHILDREN AND PETS.If swallowed, get medical help or contact a Poison Control Center right away.

DIRECTIONS

- Adults and children 12 years of age and over
- clean and dry affected area
- apply to affected area not more than 3 to 4 times daily children 12 years or younger ask a doctor

OTHER INFORMATION

- Avoid storing product in direct sunlight
- Protect product from excessive moisture
- Store with lid closed tightly

INACTIVE INGREDIENTS

Acrylates/C10-30 Alkyl Acrylate Crosspolymer, Aloe Barbadensis Leaf Juice, Citric Acid, Deionized Water, SDA 40-B Alcohol, Tromethamine

Principal Display Panel – 89 mL Container Label

FAST FREEZE®

MAXIMUM STRENGTH
LIDOCAINE
ROLL-ON

UNSCENTED

- Numbing relief
- No mess, greaseless & stain-free
- Natural ingredients include Aloe
- For the temporary relief of
  minor aches and pains of muscles
  and joints; associated with backache,
  arthritis, strains and sprains
- Paraben Free
- Plus 10% Benzyl Alcohol

3 oz (89 mL)